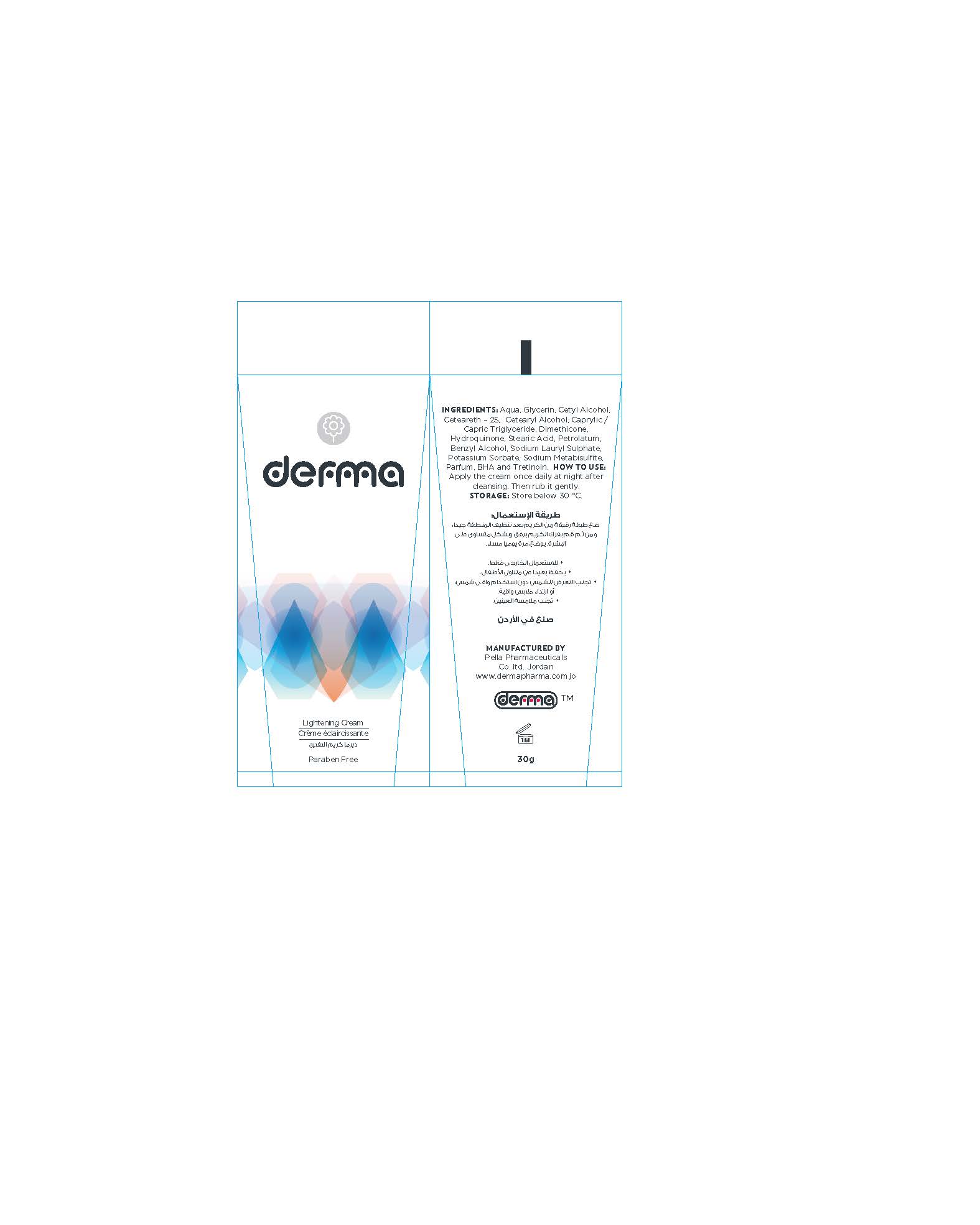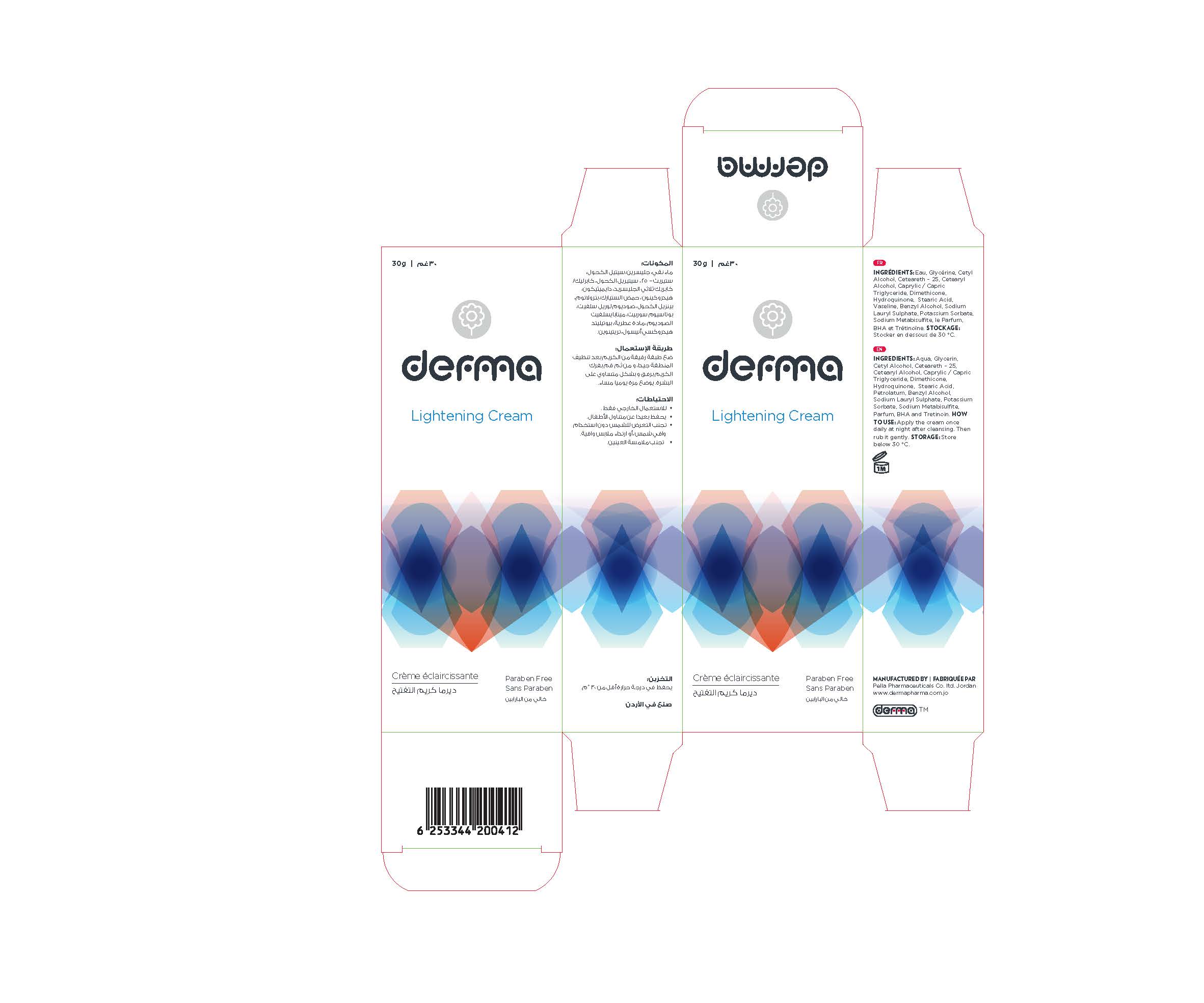 DRUG LABEL: Derma Lightening
NDC: 82160-412 | Form: CREAM
Manufacturer: Pella Pharmaceuticals Co. Ltd
Category: otc | Type: HUMAN OTC DRUG LABEL
Date: 20211201

ACTIVE INGREDIENTS: HYDROQUINONE 6 mg/30 g; TRETINOIN 0.075 mg/30 g
INACTIVE INGREDIENTS: MEDIUM-CHAIN TRIGLYCERIDES; POTASSIUM SORBATE; BUTYLATED HYDROXYANISOLE; DIMETHICONE 100; STEARIC ACID; SODIUM METABISULFITE; BENZYL ALCOHOL; SODIUM LAURYL SULFATE; PETROLATUM; WATER; GLYCERIN; CETYL ALCOHOL; CETEARETH-25; CETOSTEARYL ALCOHOL

Lightening

Forms and Presentation

Cream: Tube of 30 g.

Active Ingredients

Hydroquinone 2%

Tretinoin 0.025%

Inactive Ingredients

Aqua, Glycerin, Cetyl Alcohol, Ceteareth- 25, Cetearyl Alcohol, Caprylic / Capric Triglyceride, Dimethicone, Stearic Acid, Petrolatum, Benzyl Alcohol, Sodium Lauryl Sulphate, Potassium Sorbate, Sodium Metabisulfite, Parfum and BHA

Purpose

Lightening Cream

Properties

Night cream that lightens and moisturizes the skin.
Paraben free.

Indications

Whitening of skin.
Reduction of spots due to sunlight exposure.
Pregnancy Mask (Melasma). (Use after pregnancy)
Reduction of secular pigmentations of acne.
Can be used on knees and elbows.

Precaution

keep out of reach of children

Warnings

- For external use only
- Avoid contact with eyes
- Do not expose to sunlight and wear protective clothing

Contraindications

Hypersensitivity to any of the components.

Side effects

There are no known side effects.

Dosage and administration

Apply the cream once daily at night after cleansing. Then rub it gently.

Storage conditions

Store at a temperature be]ow 30 °C.
Do not store after a month from opening the tube.